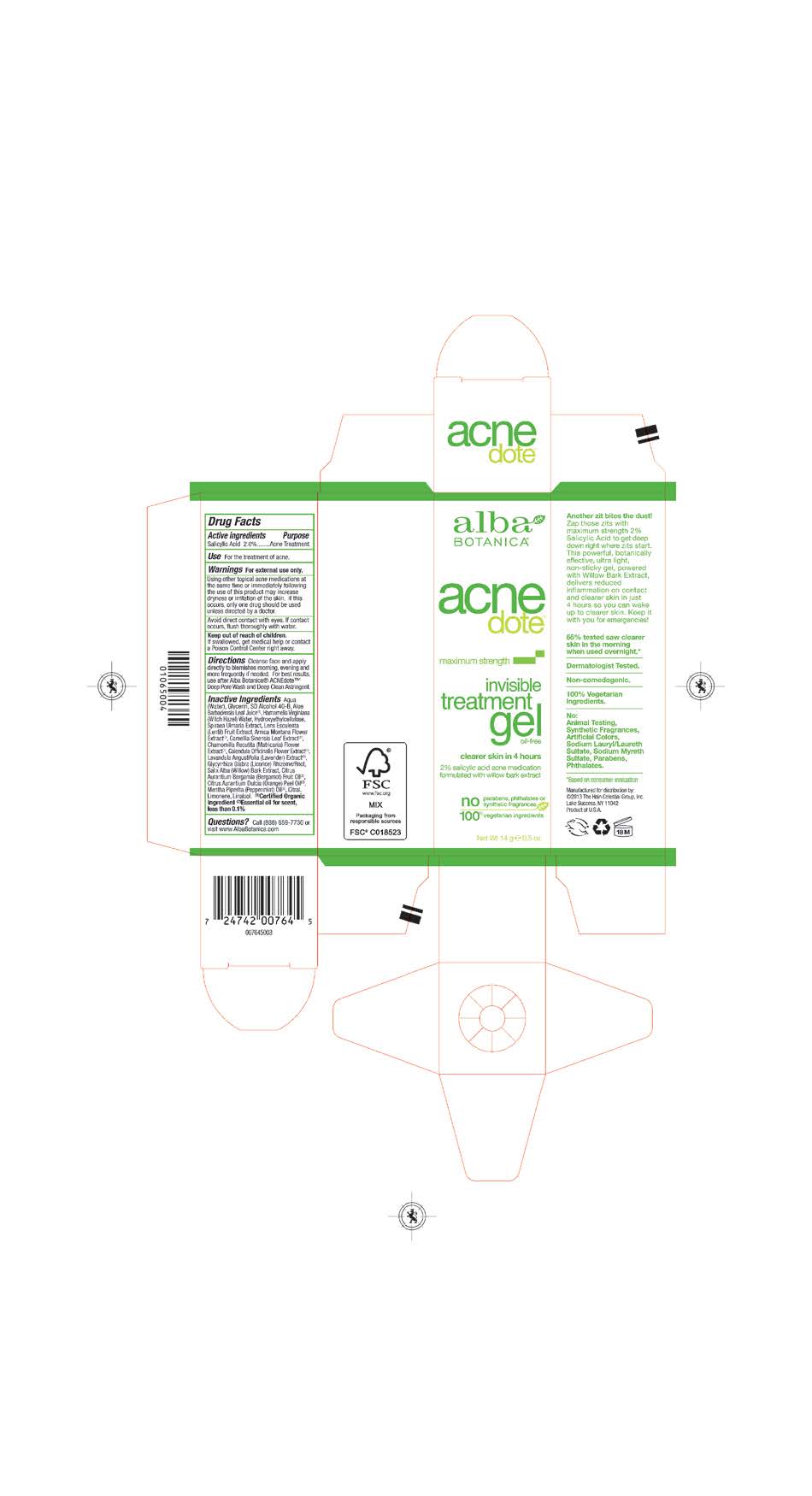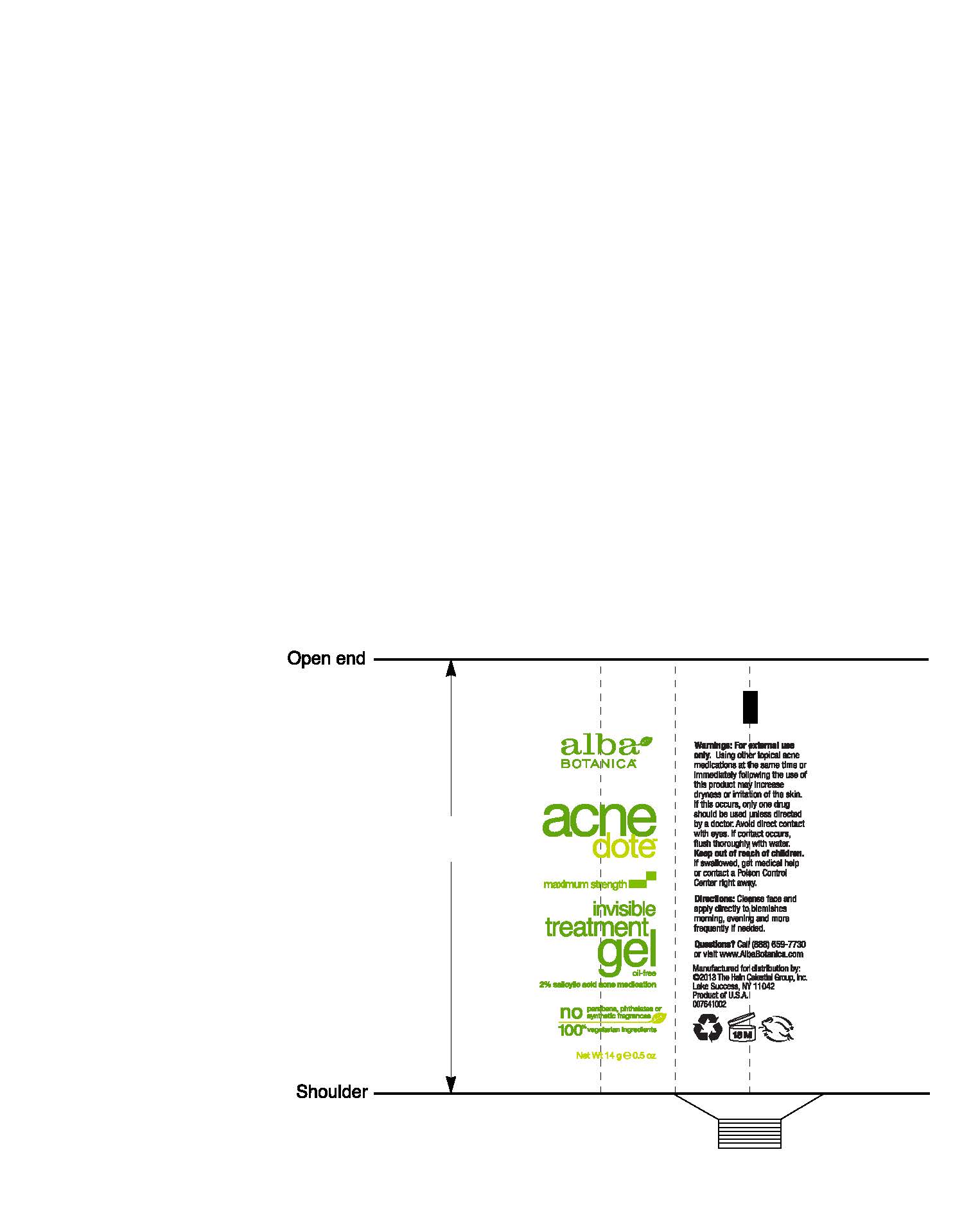 DRUG LABEL: Alba Acnedote Invisible Treatment
NDC: 61995-2764 | Form: LOTION
Manufacturer: The Hain Celestial Group, Inc.
Category: otc | Type: HUMAN OTC DRUG LABEL
Date: 20241128

ACTIVE INGREDIENTS: SALICYLIC ACID 2 g/100 g
INACTIVE INGREDIENTS: GLYCYRRHIZA GLABRA; BERGAMOT OIL; SALIX ALBA BARK; WATER; GLYCERIN; ALOE VERA LEAF; ORANGE OIL; ALCOHOL; HAMAMELIS VIRGINIANA TOP WATER; HYDROXYETHYL CELLULOSE (100 MPA.S AT 2%); FILIPENDULA ULMARIA FLOWER; LENS CULINARIS FRUIT; ARNICA MONTANA FLOWER; GREEN TEA LEAF; CALENDULA OFFICINALIS FLOWER; PEPPERMINT OIL; CHAMOMILE FLOWER OIL; LAVANDULA ANGUSTIFOLIA FLOWERING TOP

Active Ingredient

Salicylic Acid 2.0%

DOSAGE AND ADMINISTRATION

Cleanse face and apply directly to blemishes morning, evening and more frequently if needed.

PURPOSE

Acne Treatment

WARNINGS

For external use only. Using other topical acne medications at the same time or immediately following the use of this product may increase dryness and irritation of the skin. If this occurs, only one drug should be used unless directed by a doctor. Avoid direct contact with eyes. If contact occurs, flush throughly with water.

Keep out of reach of children. If swallowed get medical help or contact Poison Center right away.

INACTIVE INGREDIENT

Water, ,Glycerin, Alcohol, Aloe Barbadensis Leaf Juice(1), Hamamelis Verginiana (Witch Hazel) Water, Hydroxyethylcellulose, Spiraea Ulmaria Extract, Lens Esculenta (Lentil) Fruit Extract, Arnica Montana (Flower) Extract (1), Camellia Sinensis Leaf Extract (1), Chamomilla Recutita (Matricaria) Flower Extract (1), Calendula Officinalis Flower Extract (1), Lavandula Angustifolia (Lavender) Extract (1), Glycyrrhiza Glabra (Licorice) Rhizome/Root, Salix Alba (Willow) Bark Extract (1),Citrus Aurantium Dulcis (Orange) Peel Oil (2), Citrus Aurantium Bergamia (Bergamot) Oil (2), Mentha Piperita (Peppermint) Oil (2)

(1) Certified Organicf Ingredient; (2) Natural Fragrance

INDICATIONS AND USAGE

For the treatment of acne.